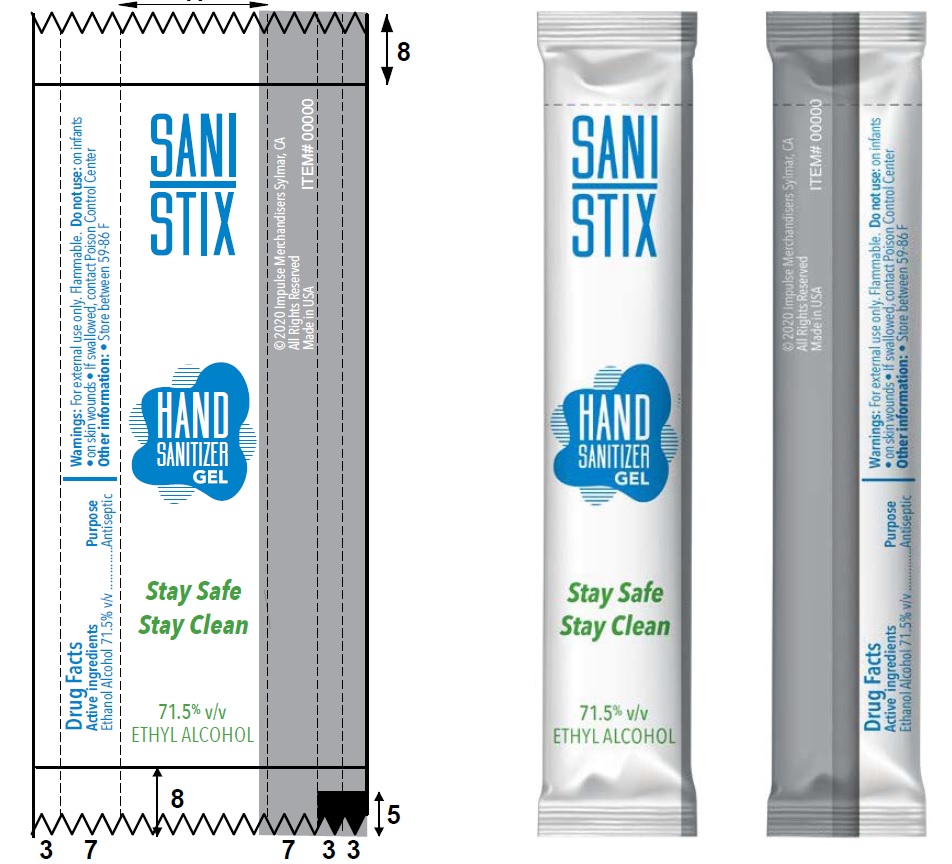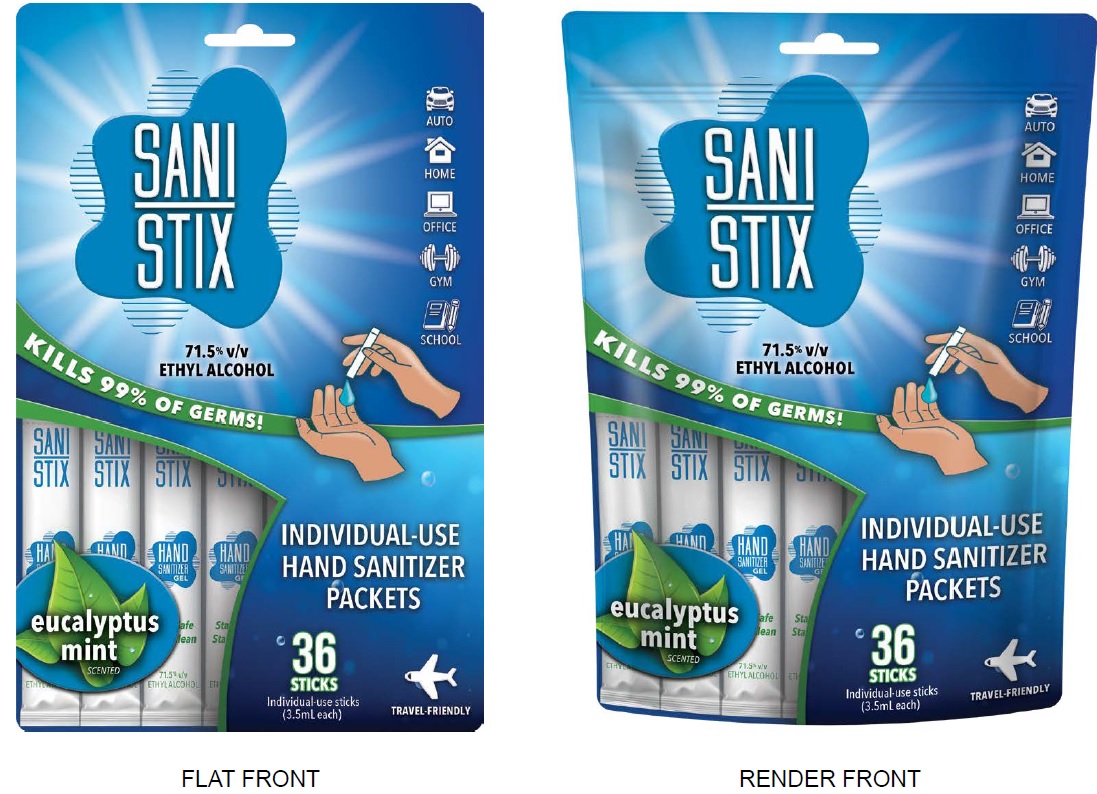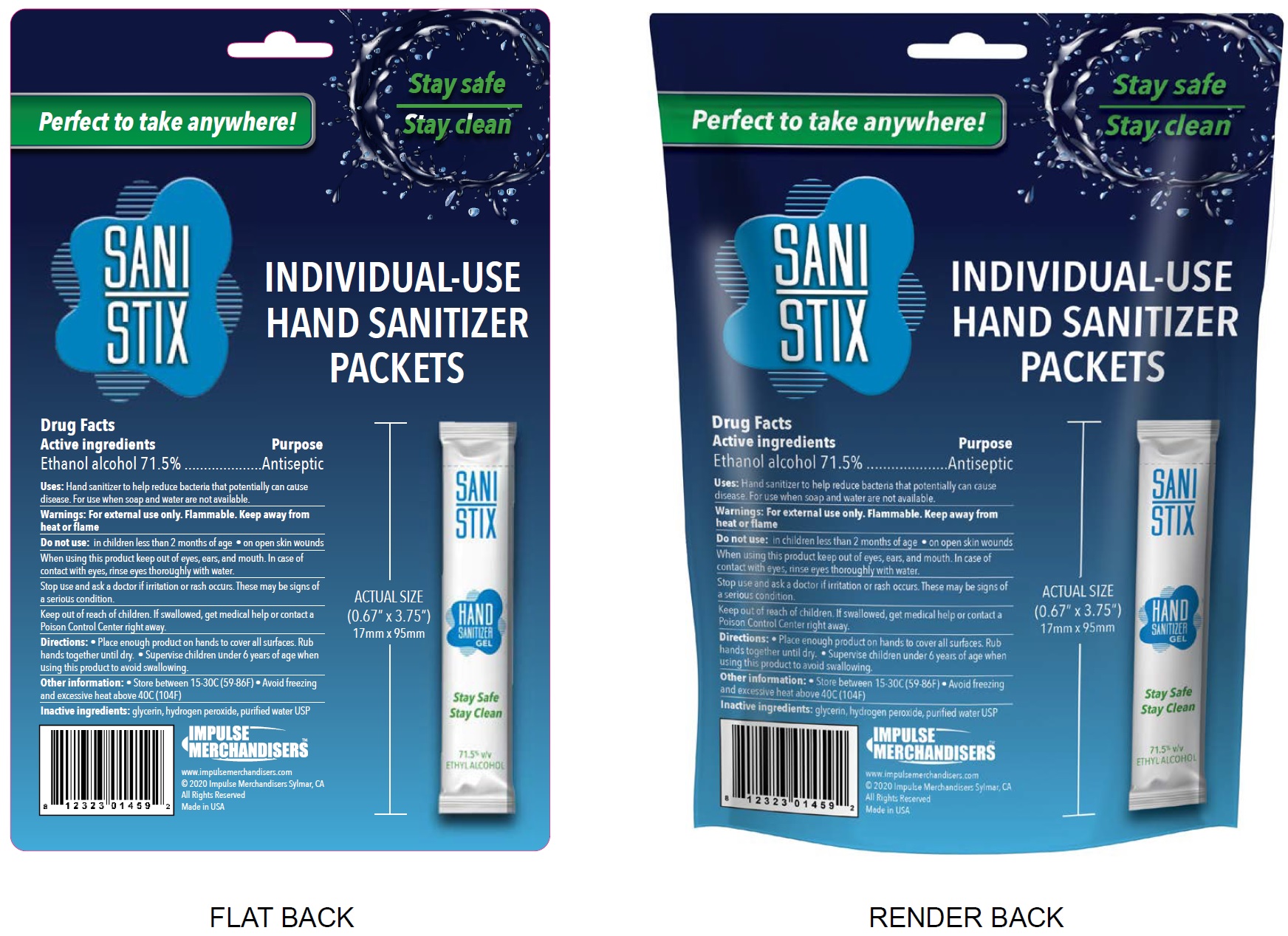 DRUG LABEL: Sani Stix
NDC: 79245-000 | Form: GEL
Manufacturer: X Auto Inc.
Category: otc | Type: HUMAN OTC DRUG LABEL
Date: 20211222

ACTIVE INGREDIENTS: ALCOHOL 0.715 mL/1 mL
INACTIVE INGREDIENTS: GLYCERIN; HYDROGEN PEROXIDE; WATER

Sani Stix

Active ingredients

Ethanol alcohol 71.5%

Purpose

Antiseptic

Uses:

Hand sanitizer to help reduce bacteria that potentially can cause disease. For use when soap and water are not available.

Warnings:

For external use only. Flammable. Keep away from heat or flame

Do not use:

in children less than 2 months of age • on open skin wounds

When using this product

keep out of eyes, ears, and mouth. In case of contact with eyes, rinse eyes thoroughly with water.

Stop use and ask a doctor

if irritation or rash occurs. These may be signs of a serious condition.

KEEP OUT OF REACH OF CHILDREN

If swallowed, get medical help or contact a Poison Control Center right away.

Directions:

• Place enough product on hands to cover all surfaces. Rub hands together until dry. • Supervise children under 6 years of age whenusing this product to avoid swallowing.

Other information:

• Store between 15-30C (59-86F) • Avoid freezing and excessive heat above 40C (104F)

Inactive ingredients:

glycerin, hydrogen peroxide, purified water USP